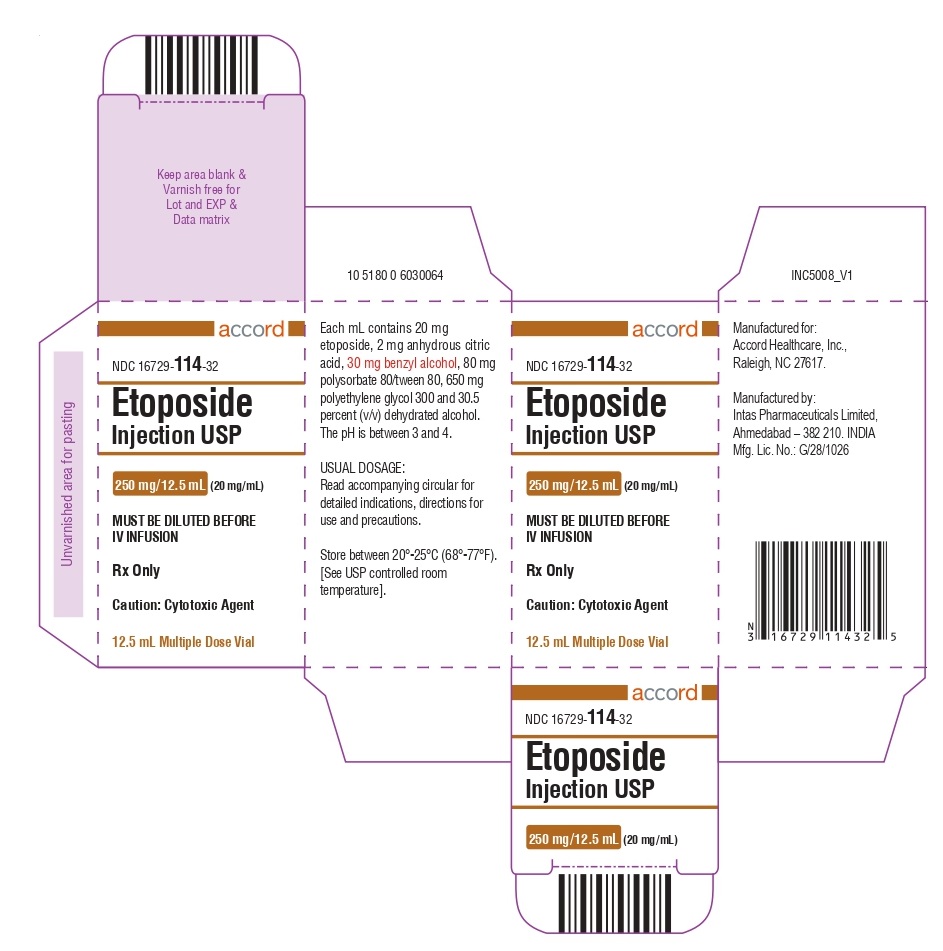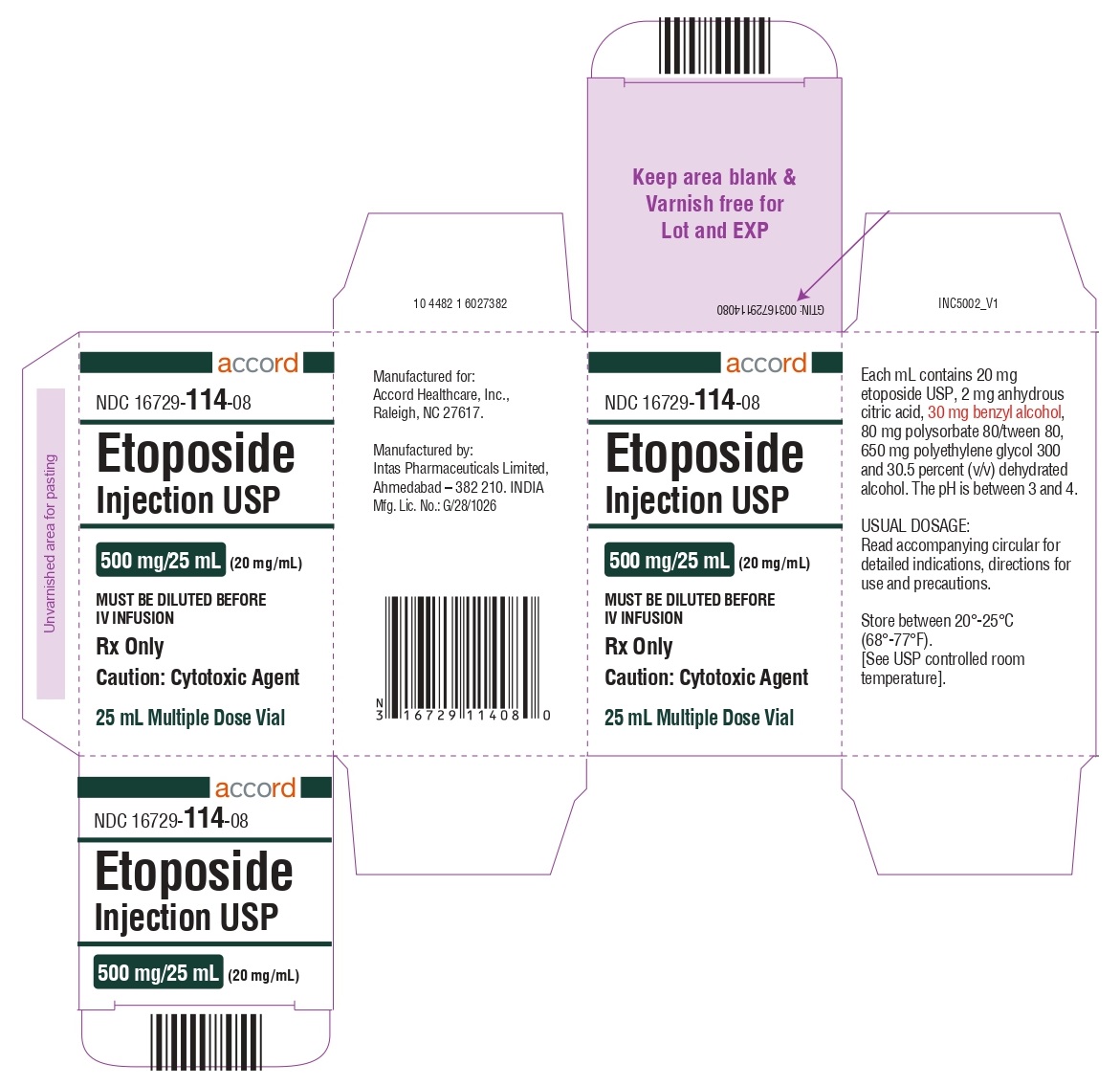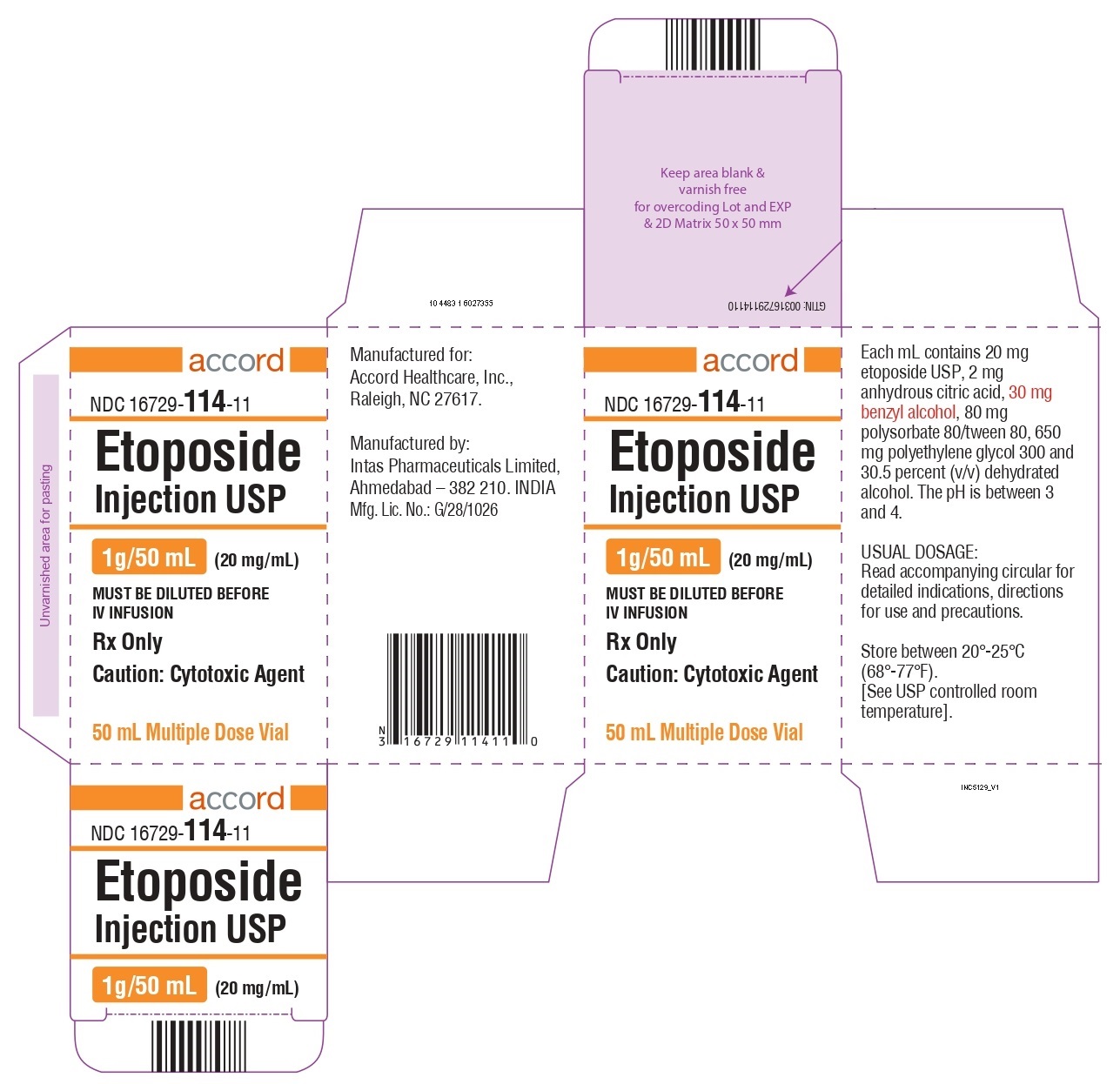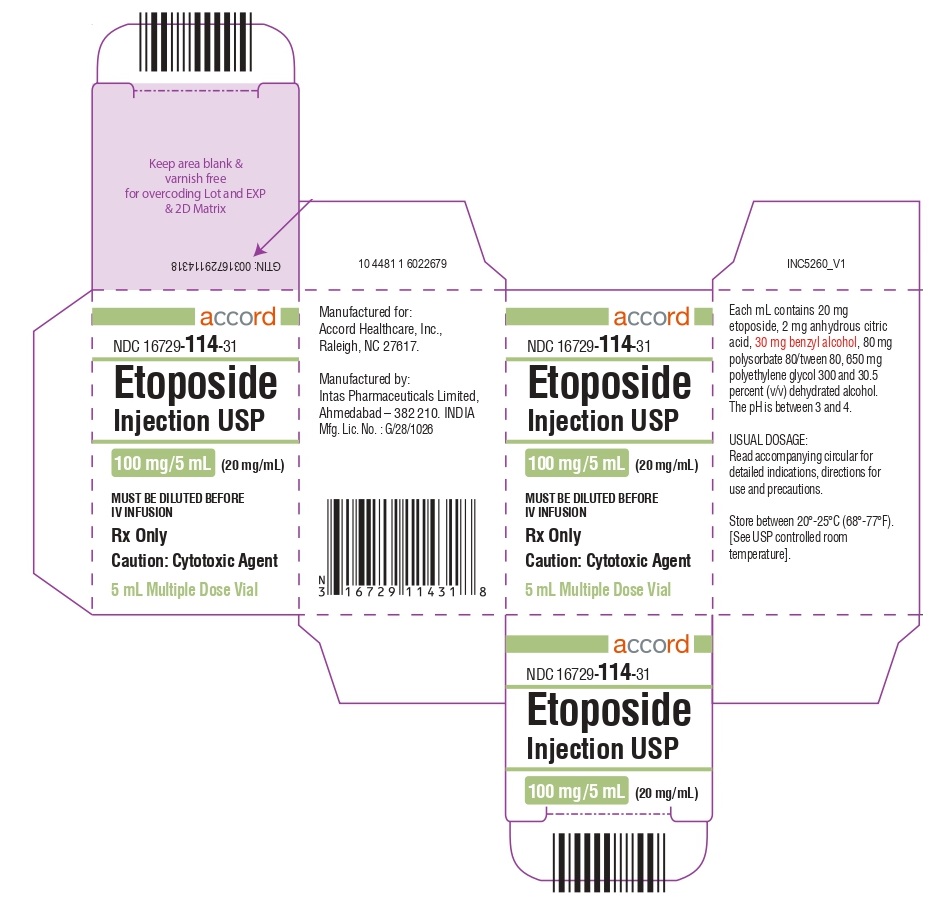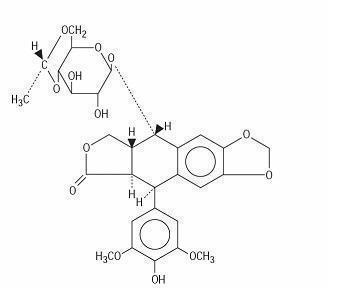 DRUG LABEL: Etoposide
NDC: 16729-114 | Form: INJECTION
Manufacturer: Accord Healthcare Inc.
Category: prescription | Type: HUMAN PRESCRIPTION DRUG LABEL
Date: 20250529

ACTIVE INGREDIENTS: ETOPOSIDE 20 mg/1 mL
INACTIVE INGREDIENTS: ALCOHOL 0.305 mL/1 mL; BENZYL ALCOHOL 30 mg/1 mL; ANHYDROUS CITRIC ACID 2 mg/1 mL; POLYSORBATE 80 80 mg/1 mL; POLYETHYLENE GLYCOL 300 650 mg/1 mL

ETOPOSIDE INJECTION USP

Rx ONLY

WARNINGS

Etoposide should be administered under the supervision of a qualified physician experienced in the use of cancer chemotherapeutic agents. Severe myelosuppression with resulting infection or bleeding may occur.

DESCRIPTION

Etoposide (also commonly known as VP-16) is a semisynthetic derivative of podophyllotoxin used in the treatment of certain neoplastic diseases. It is 4'-demethylepipodophyllotoxin 9-[4,6-O-(R)-ethylidene-β-D-glucopyranoside]. It is very soluble in methanol and chloroform, slightly soluble in ethanol and sparingly soluble in water and ether. It is made more miscible with water by means of organic solvents. It has a molecular weight of 588.58 and a molecular formula of C29H32O13.

Etoposide Injection USP is available for intravenous use as 20 mg/mL solution in 100 mg (5 mL), 250 mg (12.5 mL), 500 mg (25 mL), and 1 g (50 mL) sterile, multiple-dose vials. The pH of the clear, colorless to pale yellow liquid is 3 to 4. Each mL contains 20 mg etoposide USP, 2 mg anhydrous citric acid, 30 mg benzyl alcohol, 80 mg polysorbate 80/tween 80, 650 mg polyethylene glycol 300, and 30.5 percent (v/v) dehydrated alcohol. Vial head space contains nitrogen.

The structural formula is:

CLINICAL PHARMACOLOGY

Etoposide Injection USP has been shown to cause metaphase arrest in chick fibroblasts. Its main effect, however, appears to be at the G2 portion of the cell cycle in mammalian cells. Two different dose-dependent responses are seen. At high concentrations (10 mcg/mL or more), lysis of cells entering mitosis is observed. At low concentrations (0.3 to 10 mcg/mL), cells are inhibited from entering prophase. It does not interfere with microtubular assembly. The predominant macromolecular effect of etoposide appears to be the induction of DNA strand breaks by an interaction with DNA topoisomerase II or the formation of free radicals.

Pharmacokinetics

On intravenous administration, the disposition of etoposide is best described as a biphasic process with a distribution half-life of about 1.5 hours and terminal elimination half-life ranging from 4 to 11 hours. Total body clearance values range from 33 to 48 mL/min or 16 to 36 mL/min/m^2and, like the terminal elimination half-life, are independent of dose over a range of 100 to 600 mg/m^2. Over the same dose range, the areas under the plasma concentration vs. time curves (AUC) and the maximum plasma concentration (Cmax) values increase linearly with dose. Etoposide does not accumulate in the plasma following daily administration of 100 mg/m^2for 4 or 5 days.

The mean volumes of distribution at steady state fall in the range of 18 to 29 liters or 7 to 17 L/m^2. Etoposide enters the CSF poorly. Although it is detectable in CSF and intracerebral tumors, the concentrations are lower than in extracerebral tumors and in plasma. Etoposide concentrations are higher in normal lung than in lung metastases and are similar in primary tumors and normal tissues of the myometrium. In vitro, etoposide is highly protein bound (97%) to human plasma proteins. An inverse relationship between plasma albumin levels and etoposide renal clearance is found in children. In a study determining the effect of other therapeutic agents on the in vitrobinding of carbon-14 labeled etoposide to human serum proteins, only phenylbutazone, sodium salicylate, and aspirin displaced protein-bound etoposide at concentrations achieved in vivo.

Etoposide binding ratio correlates directly with serum albumin in patients with cancer and in normal volunteers. The unbound fraction of etoposide significantly correlated with bilirubin in a population of cancer patients. Data have suggested a significant Inverse correlation between serum albumin concentration and free fraction of etoposide. (See PRECAUTIONS.)

After intravenous administration of^14C-etoposide (100 to 124 mg/m^2), mean recovery of radioactivity in the urine was 56% of the dose at 120 hours, 45% of which was excreted as etoposide: fecal recovery of radioactivity was 44% of the dose at 120 hours.

In children, approximately 55% of the dose is excreted in the urine as etoposide in 24 hours. The mean renal clearance of etoposide is 7 to 10 mL/min/m^2or about 35% of the total body clearance over a dose range of 80 to 600 mg/m^2. Etoposide, therefore, is cleared by both renal and nonrenal processes, i.e., metabolism and biliary excretion. The effect of renal disease on plasma etoposide clearance is not known.

Biliary excretion of unchanged drug and/or metabolites is an important route of etoposide elimination as fecal recovery of radioactivity is 44% of the intravenous dose. The hydroxy acid metabolite [4’-demethylepipodophyllic acid-9-(4,6-O-(R)-ethylidene-β-D-glucopyranoside)], formed by opening of the lactone ring, is found in the urine of adults and children. It is also present in human plasma, presumably as the transisomer. Glucuronide and/or sulfate conjugates of etoposide are also excreted in human urine. Only 8% or less of an intravenous dose is excreted in the urine as radiolabeled metabolites of^14C-etoposide. In addition, O-demethylation of the dimethoxyphenol ring occurs through the CYP450 3A4 isoenzyme pathway to produce the corresponding catechol.

After intravenous infusion, the Cmax and AUC values exhibit marked intra- and inter-subject variability.

There is no evidence of a first-pass effect for etoposide. For example, no correlation exists between the absolute oral bioavailability of etoposide capsules and nonrenal clearance. No evidence exists for any other differences in etoposide metabolism and excretion after administration of oral capsules as compared to intravenous infusion.

In adults, the total body clearance of etoposide is correlated with creatinine clearance, serum albumin concentration, and nonrenal clearance. Patients with impaired renal function receiving etoposide have exhibited reduced total body clearance, increased AUC and a lower volume of distribution at steady state. (See PRECAUTIONS.) Use of cisplatin therapy is associated with reduced total body clearance. In children, elevated serum SGPT levels are associated with reduced drug total body clearance. Prior use of cisplatin may also result in a decrease of etoposide total body clearance in children.

Although some minor differences in pharmacokinetic parameters between age and gender have been observed, these differences were not considered clinically significant.

INDICATIONS AND USAGE

Etoposide Injection USP is indicated in the management of the following neoplasms:

Refractory Testicular Tumors

Etoposide Injection USP in combination therapy with other approved chemotherapeutic agents in patients with refractory testicular tumors who have already received appropriate surgical, chemotherapeutic, and radiotherapeutic therapy.

Small Cell Lung Cancer

Etoposide Injection USP in combination with other approved chemotherapeutic agents as first line treatment in patients with small cell lung cancer.

CONTRAINDICATIONS

Etoposide Injection USP is contraindicated in patients who have demonstrated a previous hypersensitivity to etoposide or any component of the formulation.

WARNINGS

Patients being treated with etoposide Injection USP must be frequently observed for myelosuppression both during and after therapy. Myelosuppression resulting in death has been reported. Dose-limiting bone marrow suppression is the most significant toxicity associated with etoposide Injection USP therapy. Therefore, the following studies should be obtained at the start of therapy and prior to each subsequent cycle of etoposide Injection USP: platelet count, hemoglobin, white blood cell count, and differential. The occurrence of a platelet count below 50,000/mm^3or an absolute neutrophil count below 500/mm^3is an indication to withhold further therapy until the blood counts have sufficiently recovered.

Physicians should be aware of the possible occurrence of an anaphylactic reaction manifested by chills, fever, tachycardia, bronchospasm, dyspnea, and hypotension. Higher rates of anaphylactic-like reactions have been reported in children who received infusions at concentrations higher than those recommended. The role that concentration of infusion (or rate of infusion) plays in the development of anaphylactic-like reactions is uncertain. (See ADVERSE REACTIONS.) Treatment is symptomatic. The infusion should be terminated immediately, followed by the administration of pressor agents, corticosteroids, antihistamines, or volume expanders at the discretion of the physician. For parenteral administration, etoposide Injection USP should be given only by slow intravenous infusion (usually over a 30- to 60-minute period), since hypotension has been reported as a possible side effect of rapid intravenous injection.

Pregnancy

Teratogenic Effects: Pregnancy Category D

Etoposide Injection USP can cause fetal harm when administered to a pregnant woman. Etoposide has been shown to be teratogenic in mice and rats.

In rats, an intravenous etoposide dose of 0.4 mg/kg/day (about 1/20th of the human dose on a mg/m^2basis) during organogenesis caused maternal toxicity, embryotoxicity, and teratogenicity (skeletal abnormalities, exencephaly, encephalocele, and anophthalmia); higher doses of 1.2 and 3.6 mg/kg/day (about 1/7th and 1/2 of human dose on a mg/m^2basis) resulted in 90 and 100% embryonic resorptions. In mice, a single 1 mg/kg (1/16th of human dose on a mg/m^2basis) dose of etoposide administered intraperitoneally on days 6, 7, or 8 of gestation caused embryotoxicity, cranial abnormalities, and major skeletal malformations. An IP dose of 1.5 mg/kg (about 1/10th of human dose on a mg/m^2basis) on day 7 of gestation caused an increase in the incidence of intrauterine death and fetal malformations and a significant decrease in the average fetal body weight.

Women of childbearing potential should be advised to avoid becoming pregnant. If this drug is used during pregnancy, or if the patient becomes pregnant while receiving this drug, the patient should be apprised of the potential hazard to the fetus.

Etoposide Injection USP should be considered a potential carcinogen in humans. The occurrence of acute leukemia with or without a preleukemic phase has been reported in rare instances in patients treated with etoposide alone or in association with other neoplastic agents. The risk of development of a preleukemic or leukemic syndrome is unclear. Carcinogenicity tests with etoposide Injection USP have not been conducted in laboratory animals.

PRECAUTIONS

General

In all instances where the use of etoposide Injection USP is considered for chemotherapy, the physician must evaluate the need and usefulness of the drug against the risk of adverse reactions. Most such adverse reactions are reversible if detected early. If severe reactions occur, the drug should be reduced in dosage or discontinued and appropriate corrective measures should be taken according to the clinical judgement of the physician. Reinstitution of etoposide Injection USP therapy should be carried out with caution and with adequate consideration of the further need for the drug and alertness as to possible recurrence of toxicity. Patients with low serum albumin may be at an increased risk for etoposide associated toxicities.

Laboratory Tests

Periodic complete blood counts should be done during the course of etoposide Injection USP treatment. They should be performed prior to each cycle of therapy and at appropriate intervals during and after therapy. At least one determination should be done prior to each dose of etoposide Injection USP.

Renal Impairment

In patients with impaired renal function, the following initial dose modification should be considered based on measured creatinine clearance:

Measured Creatinine Clearance | >50 mL/min | 15-50 mL/min
etoposide | 100% of dose | 75% of dose

Subsequent etoposide Injection USP dosing should be based on patient tolerance and clinical effect. Data are not available in patients with creatinine clearances <15 mL/min and further dose reduction should be considered in these patients.

Carcinogenesis, (see WARNINGS), Mutagenesis, Impairment of Fertility

Etoposide has been shown to be mutagenic in Ames assay.

Treatment of Swiss-Albino mice with 1.5 mg/kg IP of etoposide Injection USP on day 7 of gestation increased the incidence of intrauterine death and fetal malformations, as well as significantly decreased the average fetal body weight. Maternal weight gain was not affected.

Irreversible testicular atrophy was present in rats treated with etoposide intravenously for 30 days at 0.5 mg/kg/day (about 1/16th of the human dose on a mg/m^2basis).

Pregnancy

Teratogenic effects: Pregnancy Category D

(See WARNINGS.)

Nursing Mothers

It is not known whether this drug is excreted in human milk. Because many drugs are excreted in human milk and because of the potential for serious adverse reactions in nursing infants from etoposide Injection USP, a decision should be made whether to discontinue nursing or to discontinue the drug, taking into account the importance of the drug to the mother.

Pediatric Use

Safety and effectiveness in pediatric patients have not been established.

Etoposide Injection USP contains polysorbate 80. In premature infants, a life-threatening syndrome consisting of liver and renal failure, pulmonary deterioration, thrombocytopenia, and ascites has been associated with an injectable vitamin E product containing polysorbate 80. Anaphylactic reactions have been reported in pediatric patients (see WARNINGS).

Geriatric Use

Clinical studies of etoposide Injection USP did not include sufficient numbers of subjects aged 65 and over to determine whether they respond differently from younger subjects. Other reported clinical experience has not identified differences in responses between the elderly and younger patients. In general, dose selection for an elderly patient should be cautious, usually starting at the low end of the dosing range, reflecting the greater frequency of decreased hepatic, renal, or cardiac function, and of concomitant disease or other drug therapy.

ADVERSE REACTIONS

The following data on adverse reactions are based on intravenous administration of etoposide Injection USP as a single agent, using several different dose schedules for treatment of a wide variety of malignancies.

Hematologic Toxicity

Myelosuppression is dose-related and dose-limiting, with granulocyte nadirs occurring 7 to 14 days after drug administration and platelet nadirs occurring 9 to 16 days after drug administration. Bone marrow recovery is usually complete by day 20, and no cumulative toxicity has been reported. Fever and infection have also been reported in patients with neutropenia. Death associated with myelosuppression has been reported.

The occurrence of acute leukemia with or without a preleukemic phase has been reported rarely in patients treated with etoposide Injection USP in association with other antineoplastic agents. (See WARNINGS.)

Gastrointestinal Toxicity

Nausea and vomiting are the major gastrointestinal toxicities. The severity of such nausea and vomiting is generally mild to moderate with treatment discontinuation required in 1% of patients. Nausea and vomiting can usually be controlled with standard antiemetic therapy. Mild to severe mucositis/esophagitis may occur. Gastrointestinal toxicities are slightly more frequent after oral administration than after intravenous infusion.

Hypotension

Transient hypotension following rapid intravenous administration has been reported in 1% to 2% of patients. It has not been associated with cardiac toxicity or electrocardiographic changes. No delayed hypotension has been noted. To prevent this rare occurrence, it is recommended that etoposide Injection USP be administered by slow intravenous infusion over a 30- to 60-minute period. If hypotension occurs, it usually responds to cessation of the infusion administration of fluids or other supportive therapy as appropriate. When restarting the infusion, a slower administration rate should be used.

Allergic Reactions

Anaphylactic-like reactions characterized by chills, fever, tachycardia, bronchospasm, dyspnea, and/or hypotension have been reported to occur in 0.7% to 2% of patients receiving intravenous etoposide Injection USP and in less than 1% of the patients treated with oral capsules. These reactions have usually responded promptly to the cessation of the infusion and administration of pressor agents, corticosteroids, antihistamines, or volume expanders as appropriate; however, the reactions can be fatal. Hypertension and/or flushing have also been reported. Blood pressure usually normalizes within a few hours after cessation of the infusion. Anaphylactic-like reactions have occurred during the initial infusion of etoposide Injection USP.

Facial/tongue swelling, coughing, diaphoresis, cyanosis, tightness in throat, laryngospasm, back pain, and/or loss of consciousness have sometimes occurred in association with the above reactions. In addition, an apparent hypersensitivity-associated apnea has been reported rarely.

Rash, urticaria, and/or pruritus have infrequently been reported at recommended doses. At investigational doses, a generalized pruritic erythematous maculopapular rash, consistent with perivasculitis, has been reported.

Alopecia

Reversible alopecia, sometimes progressing to total baldness was observed in up to 66% of patients.

Other Toxicities

The following adverse reactions have been infrequently reported: abdominal pain, aftertaste, constipation, dysphagia, asthenia, fatigue, malaise, somnolence, transient cortical blindness, optic neuritis, interstitial pneumonitis/pulmonary fibrosis, fever, seizure (occasionally associated with allergic reactions), Stevens-Johnson syndrome, and toxic epidermal necrolysis, pigmentation, and a single report of radiation recall dermatitis.

Hepatic toxicity, generally in patients receiving higher doses of the drug than those recommended, has been reported with etoposide Injection USP. Metabolic acidosis has also been reported in patients receiving higher doses.

Reports of extravasation with swelling have been received postmarketing. Rarely extravasation has been associated with necrosis and venous induration.

The incidences of adverse reactions in the table that follows are derived from multiple databases from studies in 2,081 patients when etoposide was used either orally or by injection as a single agent.

ADVERSE DRUG EFFECT | PERCENT RANGE OF REPORTED INCIDENCE
Hematologic toxicity
Leukopenia (less than 1,000 WBC/mm^3) | 3–17
Leukopenia (less than 4,000 WBC/mm^3) | 60–91
Thrombocytopenia (less than 50,000 platelets/mm^3) | 1–20
Thrombocytopenia (less than 100,000 platelets/mm^3) | 22–41
Anemia | 0–33
Gastrointestinal toxicity
Nausea and vomiting | 31–43
Abdominal pain | 0–2
Anorexia | 10–13
Diarrhea | 1–13
Stomatitis | 1–6
Hepatic | 0–3
Alopecia | 8–66
Peripheral neurotoxicity | 1–2
Hypotension | 1–2
Allergic reaction | 1–2

OVERDOSAGE

No proven antidotes have been established for etoposide Injection USP overdosage.

DOSAGE AND ADMINISTRATION

Note: Plastic devices made of acrylic or ABS (a polymer composed of acrylonitrile, butadiene, and styrene) have been reported to crack and leak when used with undilutedEtoposide Injection USP.

The usual dose of Etoposide Injection USP in testicular cancer in combination with other approved chemotherapeutic agents ranges from 50 to 100 mg/m^2/day on days 1 through 5 to 100 mg/m^2/day on days 1, 3, and 5.

In small cell lung cancer, the Etoposide Injection USP dose in combination with other approved chemotherapeutic drugs ranges from 35 mg/m^2/day for 4 days to 50 mg/m^2/day for 5 days.

For recommended dosing adjustments in patients with renal impairment see PRECAUTIONS.

Chemotherapy courses are repeated at 3- to 4-week intervals after adequate recovery from any toxicity.

The dosage should be modified to take into account the myelosuppressive effects of other drugs in the combination or the effects of prior X-ray therapy or chemotherapy which may have compromised bone marrow reserve.

Administration Precautions

As with other potentially toxic compounds, caution should be exercised in handling and preparing the solution of etoposide. Skin reactions associated with accidental exposure to Etoposide Injection USP may occur. The use of gloves is recommended. If etoposide solution contacts the skin or mucosa, immediately and thoroughly wash the skin with soap and water and flush the mucosa with water.

Preparation for Intravenous Administration

Etoposide Injection USP must be diluted prior to use with either 5% Dextrose Injection, or 0.9% Sodium Chloride Injection, to give a final concentration of 0.2 to 0.4 mg/mL. If solutions are prepared at concentrations above 0.4 mg/mL, precipitation may occur. Hypotension following rapid intravenous administration has been reported; hence, it is recommended that the etoposide Injection USP solution be administered over a 30- to 60-minute period. A longer duration of administration may be used if the volume of fluid to be infused is a concern.

Etoposide Injection USP should not be given by rapid intravenous injection.

Parenteral drug products should be inspected visually for particulate matter and discoloration (see DESCRIPTION) prior to administration whenever solution and container permit.

Stability

Unopened vials of Etoposide Injection USP are stable for 24 months at room temperature (25°C). Vials diluted as recommended to a concentration of 0.2 or 0.4 mg/mL are stable for 96 and 24 hours, respectively, at room temperature (25°C) under normal room fluorescent light in both glass and plastic containers.

Procedures for proper handling and disposalof anticancer drugs should be considered. Several guidelines on this subject have been published.^1–7There is no general agreement that all of the procedures recommended in the guidelines are necessary or appropriate.

HOW SUPPLIED

Etoposide Injection USP, 20 mg/mL, is supplied as follows:

NDC 16729-114-31 100 mg/5 mL Sterile, Multiple Dose Vial.

NDC 16729-114-32 250 mg/12.5 mL Sterile, Multiple Dose Vial

NDC 16729-114-08 500 mg/25 mL Sterile, Multiple Dose Vial.

NDC 16729-114-11, 1 g/50 mL Sterile, Multiple Dose Vial.

Store between 20° to 25°C (68° to 77°F). See USP controlled room temperature.

REFERENCES

1. Recommendations for the Safe Handling of Parenteral Antineoplastic Drugs. NIH Publication No. 83-2621. For sale by the Superintendent of Documents, US Government Printing Office, Washington, DC 20402.
2. AMA Council Report. Guidelines for Handling Parenteral Antineoplastics. JAMA1985 March 15.
3. National Study Commission on Cytotoxic Exposure - Recommendations for Handling Cytotoxic Agents. Available from Louis P. Jeffrey, Sc.D., Chairman, National Study Commission on Cytotoxic Exposure, Massachusetts College of Pharmacy and Allied Health Sciences, 179 Longwood Avenue, Boston, Massachusetts 02115.
4. Clinical Oncological Society of Australia. Guidelines and Recommendations for Safe Handling of Antineoplastic Agents. Med J Australia1:426-428, 1983.
5. Jones RB, et al. Safe handling of chemotherapeutic agents: A report from the Mount Sinai Medical Center. CA - A Cancer Journal for Clinicians(Sept/Oct):258–263, 1983.
6. American Society of Hospital Pharmacists Technical Assistance Bulletin on Handling Cytotoxic and Hazardous Drugs. Am J Hosp Pharm47:1033–1049, 1990.
7. Controlling Occupational Exposure to Hazardous Drugs. (OSHA Work-Practice Guidelines). Am J Health-Syst Pharm53:1669–1685, 1996.

Manufactured for:
Accord Healthcare, Inc.
8041 Arco Corporate Drive,
Suite 200,
Raleigh, NC 27617,
USA.

Manufactured by:
Intas Pharmaceuticals Limited,
Plot No.: 457, 458, Village – Matoda
Bavla Road, Ta. – Sanand,
Dist. – Ahmedabad – 382 210. India
Issued - November, 2023
10 7120 1 6029027